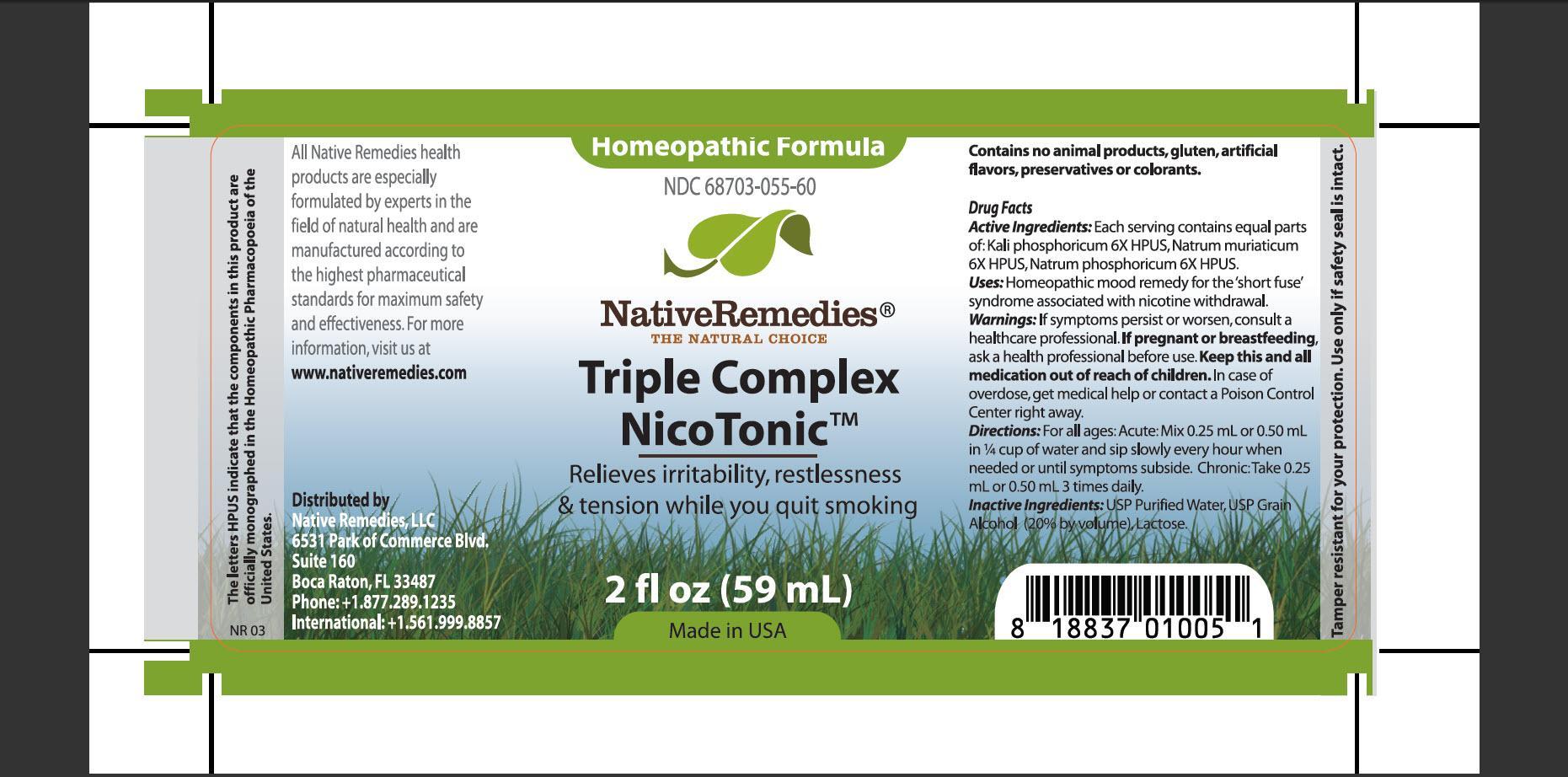 DRUG LABEL: Triple Complex NicoTonic
NDC: 68703-055 | Form: TINCTURE
Manufacturer: Native Remedies, LLC
Category: homeopathic | Type: HUMAN OTC DRUG LABEL
Date: 20130403

ACTIVE INGREDIENTS: POTASSIUM PHOSPHATE, DIBASIC 6 [hp_X]/1 mL; SODIUM CHLORIDE 6 [hp_X]/1 mL; SODIUM PHOSPHATE, DIBASIC, HEPTAHYDRATE 6 [hp_X]/1 mL
INACTIVE INGREDIENTS: WATER; ALCOHOL; LACTOSE

Triple Complex NicoTonic

PURPOSE

Relieves irritability, restlessness and tension while you quit smoking

ACTIVE INGREDIENT

Active Ingredients: Each serving contains equal parts of: Kali phosphoricum 6X HPUS, Natrum muriaticum 6X HPUS, Natrum phosphoricum 6X HPUS

INDICATIONS AND USAGE

Uses: Homeopathic mood remedy for the 'short fuse' syndrome associated with nicotine withdrawal

WARNINGS

Warnings: If symptoms persist or worsen, consult a healthcare professional

PREGNANCY OR BREAST FEEDING

If pregnant or breastfeeding, ask a healthcare professional before use

KEEP OUT OF REACH OF CHILDREN

Keep this and all medication out of reach of children

OVERDOSAGE

In case of overdose, get medical help or contact a Poison Control Center right away

DOSAGE AND ADMINISTRATION

Directions: For all ages: Acute: Mix0.25 mL or 0.50 mL in 1/4 cup of water and sip slowly every hour when needed or until symptoms subside. Chronic: Take 0.25 mL or 0.50 mL 3 times daily

INACTIVE INGREDIENT

Inactive Ingredients: USP Purified Water, USP Grain Alcohol (20% by volume), Lactose

PATIENT COUNSELING INFORMATION

The letters HPUS indicate that the components in this product are officially monographed in the Homeopathic Pharmacopoeia of the United States

All Native Remedies health products are especially formulated by experts in the field of natural health and are manufactured according to the highest pharmaceutical standards for maximum safety and effectiveness. For more information, visit us at www.nativeremedies.com

Distributed by
Native Remedies, LLC
6531 Park of Commerce Blvd.
Suite 160
Boca Raton, FL 33487
Phone: +1.877.289.1235
International: +1.561.999.8857

Contains no animal products, gluten, artificial flavors, preservatives or colorants

STORAGE AND HANDLING

Tamper resistant for your protection. Use only if safety seal is intact